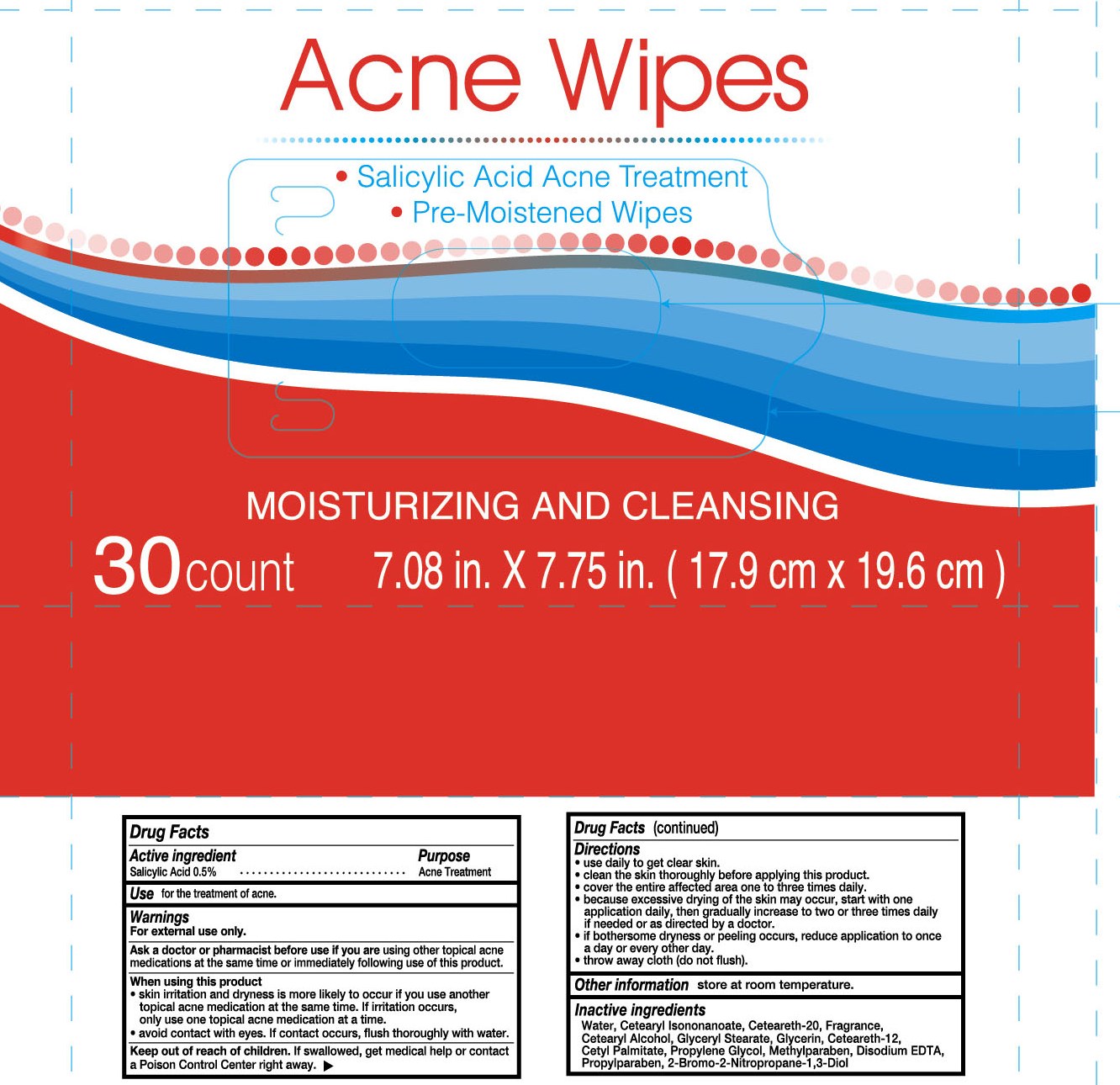 DRUG LABEL: Acne Wipes
NDC: 69733-566 | Form: SWAB
Manufacturer: JIANGSU TERRA MEDICAL TECHNOLOGY CO LTD
Category: otc | Type: HUMAN OTC DRUG LABEL
Date: 20150929

ACTIVE INGREDIENTS: SALICYLIC ACID 5 mg/1000 mg
INACTIVE INGREDIENTS: PROPYLENE GLYCOL; WATER; CETEARYL ISONONANOATE; CETEARETH-2 PHOSPHATE; GLYCERIN; CETOSTEARYL ALCOHOL; GLYCERYL STEARATE SE; CETEARETH-12; CETYL PALMITATE; METHYLPARABEN; DISODIUM EDTA-COPPER; BRONOPOL; PROPYLPARABEN

Active ingredient

Sallcylic Acid 0.5%

Purpose

acne treatment

Use

for the treatment of acne.

Warnings

for external use only

ask a doctor or pharmacist before use if you are using other topical acne medications at the same time or immediately

over large areas of the body following use of this product.

When using this product

skin irritation and dryness is more likely to occur if you use another topical acne medication at the same time .if irritation occurs,only use one topical acne medication at a time.

avoid contact with eyes,if contact occurs ,flush thoroughly with water.

Keep out of reach of children .if swallowed,get medical help or contact a Poison Control Center reght away.

Keep out of reach of children ,If swallowed ,get medical help or contact a Poison Control Center right away.

Directions

use daily to get clear skin.

clean the skin thoroughly before applying this product.

cover the entire affected area one to three times daily.

because excessive drying of the skin may occur,start with one application daily ,then gradually increase to two or three times daily if needed or as directed by a doctor .

if bothersome dryness or peeling occurs ,reduce application to once a day or every other day.

throw away cloth(do not flush)

INACTIVE INGREDIENT

water ,cetearyl isononaneate,ceteareth-20,fregrance,cetearyl alcohol,glyceryl stearate,glycerin,ceteareth-12,cetyl palmitate,proplyene glycol,methjylparaben,disodium EDTA,propylparaben,2-bromo-2-nitropropane-1,3-Diol